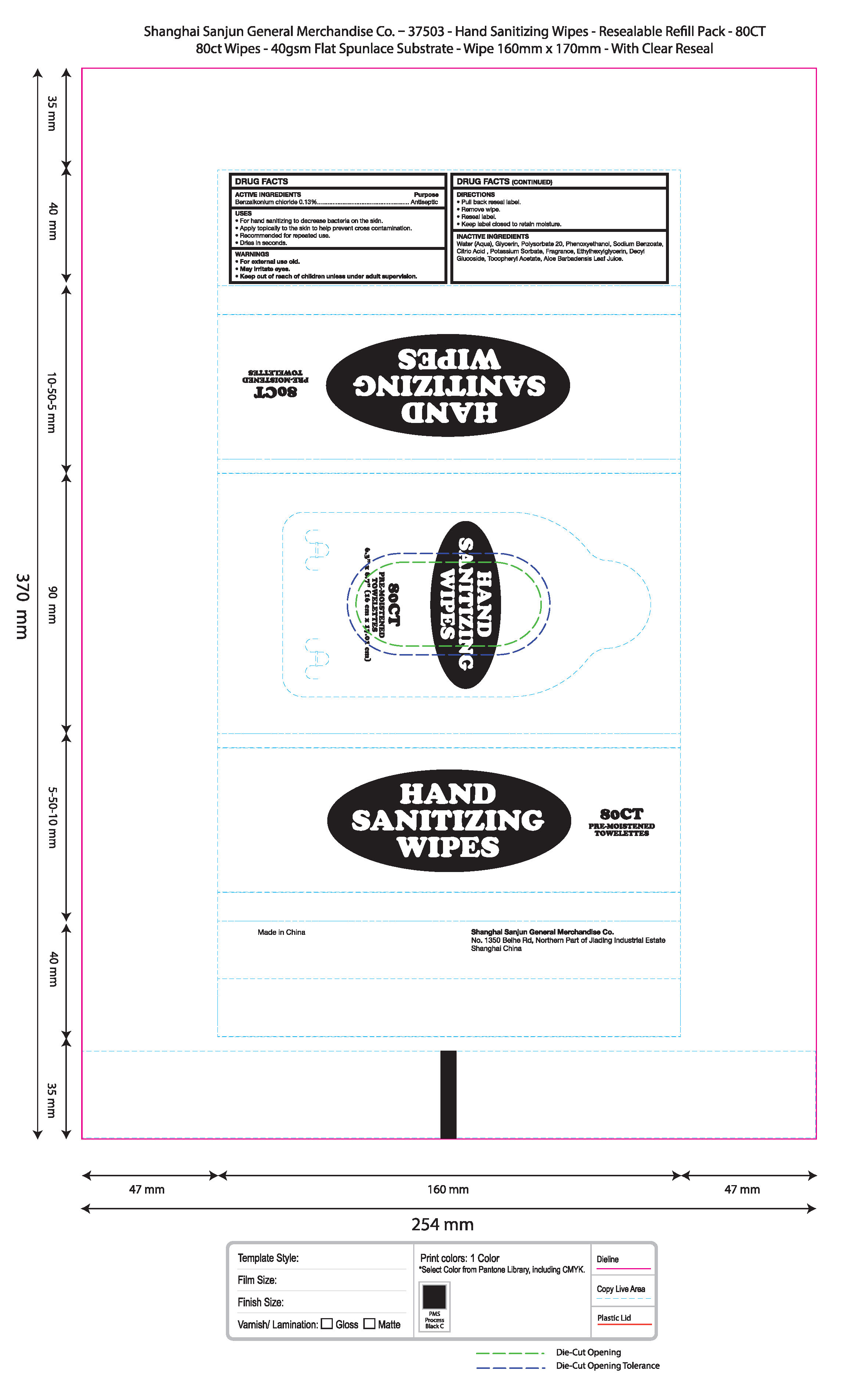 DRUG LABEL: Hand Sanitizing Wipes 80CT
NDC: 75670-004 | Form: CLOTH
Manufacturer: SHANGHAI SANJUN GENERAL MERCHANDISE CO., LTD.
Category: otc | Type: HUMAN OTC DRUG LABEL
Date: 20220224

ACTIVE INGREDIENTS: BENZALKONIUM CHLORIDE 0.13 g/100 g
INACTIVE INGREDIENTS: DECYL GLUCOSIDE; ALPHA-TOCOPHEROL ACETATE; PHENOXYETHANOL; WATER; SODIUM BENZOATE; ETHYLHEXYLGLYCERIN; POLYSORBATE 20; GLYCERIN; ALOE VERA FLOWER; CITRIC ACID MONOHYDRATE; POTASSIUM SORBATE

75670-004 Hand sanitizing wipes 80CT 0.13%Benzalkonium Chloride

Active Ingredient

Benzalkonium Chloride 0. 13 %

PURPOSE

Antiseptic

USE

●For hand sanitizing to decrease bacteria on the skin.
●Apply topically to the skin to help prevent cross contamination.
●Recommended for repeated use.
Dries in seconds.

Warning

●For extemal use only
●May iritate eyes

Keep out of reach of children unless under
adult supervision

Directions

●Pull back reseal label.
●Remove wipe.
。Reseal label.
●Keep label closed ro retain moisture.

Inactive ingredients

Water (Aqua), Glycerin, Polysorbate 20, Phenoxyethanol, Sodium Benzoate,
Citric Acid , Potassium Sorbate, Fragrance, Ethylhexylglycerin, Decyl
Glucoside, Tocopheryl Acetate, Aloe Barbadensis Leaf Juice.